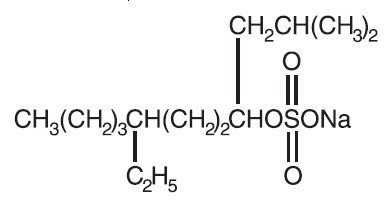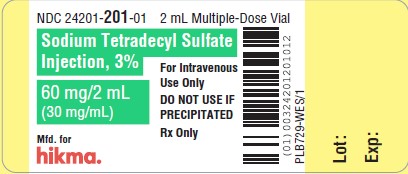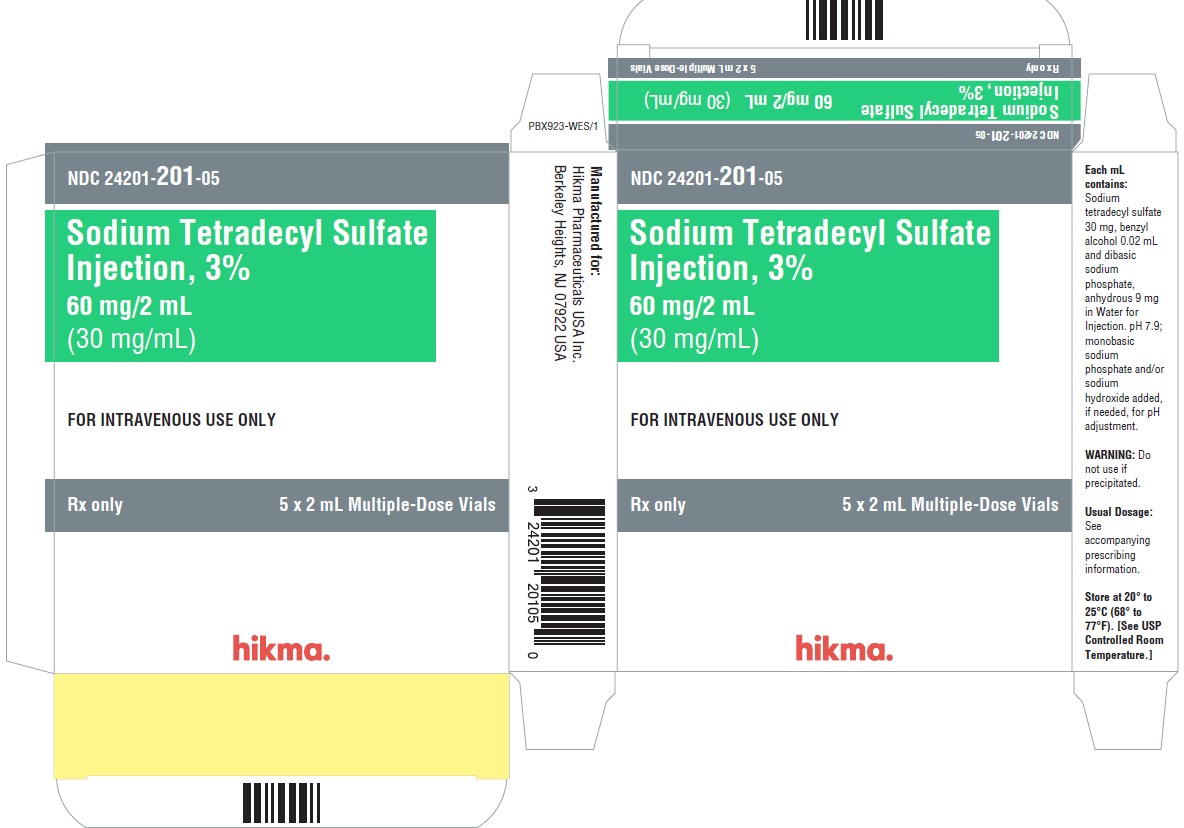 DRUG LABEL: Sodium Tetradecyl Sulfate
NDC: 24201-201 | Form: INJECTION, SOLUTION
Manufacturer: Hikma Pharmaceuticals USA Inc.
Category: prescription | Type: HUMAN PRESCRIPTION DRUG LABEL
Date: 20240626

ACTIVE INGREDIENTS: SODIUM TETRADECYL SULFATE 30 mg/1 mL
INACTIVE INGREDIENTS: BENZYL ALCOHOL 0.02 mL/1 mL; SODIUM PHOSPHATE, DIBASIC, ANHYDROUS 9 mg/1 mL; WATER

Sodium Tetradecyl Sulfate Injection, 3%
60 mg/2 mL (30 mg/mL)
FOR INTRAVENOUS USE ONLY
Rx only

DESCRIPTION

Sodium tetradecyl sulfate is an anionic surfactant which occurs as a white, waxy solid. The structural formula is as follows:

C14H29NaSO4 7-Ethyl-2-methyl-4-hendecanol sulfate sodium salt MW 316.44

Sodium tetradecyl sulfate injection is a sterile nonpyrogenic solution for intravenous use as a sclerosing agent.

3% 60 mg/2 mL (30 mg/mL): Each mL contains sodium tetradecyl sulfate 30 mg, benzyl alcohol 0.02 mL and dibasic sodium phosphate, anhydrous 9 mg in Water for Injection. pH 7.9; monobasic sodium phosphate and/or sodium hydroxide added, if needed, for pH adjustment.

CLINICAL PHARMACOLOGY

Sodium tetradecyl sulfate injection is a sclerosing agent. Intravenous injection causes intima inflammation and thrombus formation. This usually occludes the injected vein. Subsequent formation of fibrous tissue results in partial or complete vein obliteration that may or may not be permanent.

INDICATIONS AND USAGE

Sodium tetradecyl sulfate injection is indicated in the treatment of small uncomplicated varicose veins of the lower extremities that show simple dilation with competent valves. The benefit- to-risk ratio should be considered in selected patients who are great surgical risks.

CONTRAINDICATIONS

Sodium tetradecyl sulfate injection is contraindicated in previous hypersensitivity reactions to the drug; in acute superficial thrombophlebitis; valvular or deep vein incompetence; huge superficial veins with wide open communications to deeper veins; phlebitis migrans; acute cellulitis; allergic conditions; acute infections; varicosities caused by abdominal and pelvic tumors unless the tumor has been removed; bedridden patients; such uncontrolled systemic diseases as diabetes, toxic hyperthyroidism, tuberculosis, asthma, neoplasm, sepsis, blood dyscrasias and acute respiratory or skin diseases.

WARNINGS

Sodium tetradecyl sulfate injection should only be administered by a healthcare professional experienced in venous anatomy and the diagnosis and treatment of conditions affecting the venous system and familiar with proper injection technique. Severe adverse local effects, including tissue necrosis, may occur following extravasation; therefore, extreme care in intravenous needle placement and using the minimal effective volume at each injection site are important.

Emergency resuscitation equipment should be immediately available. Allergic reactions, including fatal anaphylaxis, have been reported. As a precaution against anaphylactic shock, it is recommended that 0.5 mL of sodium tetradecyl sulfate injection be injected into a varicosity, followed by observation of the patient for several hours before administration of a second or larger dose. The possibility of an anaphylactic reaction should be kept in mind, and the physician should be prepared to treat it appropriately.

Because of the danger of thrombosis extension into the deep venous system, thorough preinjection evaluation for valvular competency should be carried out and slow injections with a small amount (not over 2 mL) of the preparation should be injected into the varicosity. Deep venous patency must be determined by noninvasive testing such as duplex ultrasound. Venous sclerotherapy should not be undertaken if tests such as Trendelenberg and Perthes, and angiography show significant valvular or deep venous incompetence.

The development of deep vein thrombosis and pulmonary embolism have been reported following sclerotherapy treatment of superficial varicosities. Patients should have post-treatment follow-up of sufficient duration to assess for the development of deep vein thrombosis. Embolism may occur as long as four weeks after injection of sodium tetradecyl sulfate. Adequate post-treatment compression may decrease the incidence of deep vein thrombosis.

Arterial Embolism

Stroke, transient ischemic attack, myocardial infarction, and impaired cardiac function have been reported in close temporal relationship with STS administration. These events may be caused by air embolism when using the product foamed with room air (high nitrogen concentration) or thromboembolism. The safety and efficacy of STS foamed with room air has not been established and its use should be avoided.

PRECAUTIONS

GENERAL

Extreme caution must be exercised in the presence of underlying arterial disease such as marked peripheral arteriosclerosis or thromboangiitis obliterans (Buerger’s Disease).

DRUG INTERACTIONS

No well-controlled studies have been performed on patients taking antiovulatory agents. The physician must use judgment and evaluate any patient taking antiovulatory drugs prior to initiating treatment with sodium tetradecyl sulfate injection. (See ADVERSE REACTIONS section.)

Heparin should not be included in the same syringe as sodium tetradecyl sulfate injection, since the two are incompatible.

CARCINOGENESIS, MUTAGENESIS, IMPAIRMENT OF FERTILITY

When tested in the L5178YTK +/- mouse lymphoma assay, sodium tetradecyl sulfate did not induce a dose-related increase in the frequency of thymidine kinase-deficient mutants and, therefore, was judged to be nonmutagenic in this system. However, no long-term animal carcinogenicity studies with sodium tetradecyl sulfate have been performed.

PREGNANCY

Teratogenic Effects

Animal reproduction studies have not been conducted with sodium tetradecyl sulfate injection. It is also not known whether sodium tetradecyl sulfate injection can cause fetal harm when administered to a pregnant woman or can affect reproduction capacity. sodium tetradecyl sulfate injection should be given to a pregnant woman only if clearly needed and the benefits outweigh the risks.

NURSING MOTHERS

It is not known whether this drug is excreted in human milk. Because many drugs are excreted in human milk, caution should be exercised when sodium tetradecyl sulfate injection is administered to a nursing woman.

PEDIATRIC USE

Safety and effectiveness in pediatric patients have not been established.

ADVERSE REACTIONS

Local reactions consisting of pain, urticaria or ulceration may occur at the site of injection. A permanent discoloration may remain along the path of the sclerosed vein segment. Sloughing and necrosis of

tissue may occur following extravasation of the drug. (See WARNINGS section.)

Allergic reactions such as hives, asthma, hay fever and anaphylactic shock have been reported. Mild systemic reactions that have been reported include headache, nausea and vomiting. (See WARNINGS section.)

At least six deaths have been reported with the use of sodium tetradecyl sulfate injection. Four cases of anaphylactic shock leading to death have been reported in patients who received sodium tetradecyl sulfate injection. One of these four patients reported a history of asthma, a contraindication to the administration of sodium tetradecyl sulfate injection. (See WARNINGS section.)

One death has been reported in a patient who received sodium tetradecyl sulfate injection and who had been receiving an antiovulatory agent. Another death (fatal pulmonary embolism) has been reported in a 36-year-old female treated with sodium tetradecyl acetate and who was not taking oral contraceptives.

Cerebrovascular accident, myocardial infarction

To report SUSPECTED ADVERSE REACTIONS, contact Hikma Pharmaceuticals USA Inc. at 1-877-845-0689 or FDA at 1-800 FDA-1088 or www.fda.gov/medwatch.

DOSAGE AND ADMINISTRATION

Parenteral drug products should be inspected visually for particulate matter and discoloration prior to administration. Do not use if precipitated or discolored.

Sodium tetradecyl sulfate injection is for intravenous use only. The strength of solution required depends on the size and degree of varicosity. In general, the 1% solution will be found most useful with the 3% solution preferred for larger varicosities. The dosage should be kept small, using 0.5 mL to 2 mL (preferably 1 mL maximum) for each injection, and the maximum single treatment should not exceed 10 mL.

HOW SUPPLIED

Sodium tetradecyl sulfate injection, 3%, 60 mg/2 mL (30 mg/mL) is a sterile nonpyrogenic solution for intravenous use.

NDC 24201-201-05
Carton containing 5 x 2 mL multiple-dose vials.

STORAGE

Store at 20° to 25°C (68° to 77°F). [See USP Controlled Room Temperature.]

ANIMAL TOXICOLOGY

The intravenous LD50 of sodium tetradecyl sulfate in mice was reported to be 90 ± 5 mg/kg.

In the rat, the acute intravenous LD50 of sodium tetradecyl sulfate was estimated to be between 72 mg/kg and 108 mg/kg.

Purified sodium tetradecyl sulfate was found to have an LD50 of 2 g/kg when administered orally by stomach tube as a 25% aqueous solution to rats. In rats given 0.15 g/kg in drinking water for 30 days, no appreciable toxicity was seen, although some growth inhibition was discernible.

Manufactured for:
Hikma Pharmaceuticals USA Inc.
Berkeley Heights, NJ 07922 USA

Manufactured by:
Hikma Farmacêutica (Portugal), S.A.
Estrada do Rio da Mó, 8, 8A e 8B - Fervença
2705-906 Terrugem SNT, PORTUGAL

REVISED December 2023
PIN657-WES/1

PRINCIPAL DISPLAY PANEL - 30 mg/mL Carton Label

NDC 24201- 201-01

2 mL Multiple-Dose Vial

Sodium Tetradecyl Sulfate 3%
Injection

60 mg/2 mL
(30 mg/mL)

FOR IV USE ONLY

DO NOT USE IF
PRECIPITATED

Rx Only

NDC 24201- 201-05

5 x 2 mL Multiple-Dose Vial

Sodium Tetradecyl Sulfate 3%
Injection

60 mg/2 mL
(30 mg/mL)

FOR IV USE ONLY

DO NOT USE IF
PRECIPITATED

Rx Only